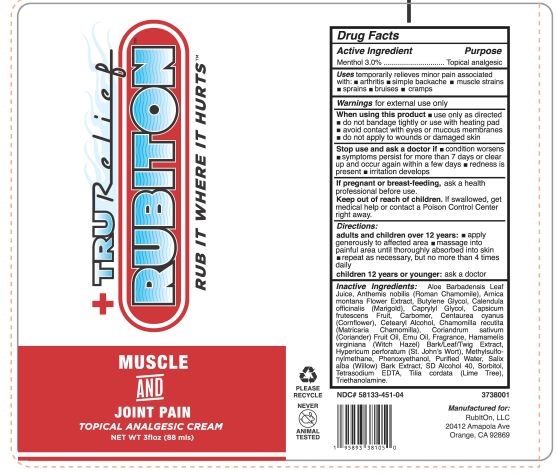 DRUG LABEL: TruRelief RUBITON Rub It Where It Hurts
NDC: 58133-451 | Form: CREAM
Manufacturer: Cosmetic Specialty Labs, Inc.
Category: otc | Type: HUMAN OTC DRUG LABEL
Date: 20220208

ACTIVE INGREDIENTS: MENTHOL 3 g/100 mL
INACTIVE INGREDIENTS: CAPSICUM; EMU OIL; ALOE VERA LEAF; ARNICA MONTANA FLOWER; CORIANDER OIL; TILIA CORDATA FLOWER; DEHYDRATED ALCOHOL; HAMAMELIS VIRGINIANA TOP; HYPERICUM PERFORATUM; DIMETHYL SULFONE; SALIX ALBA BARK; EDETATE SODIUM TETRAHYDRATE; CHAMAEMELUM NOBILE FLOWER; CAPRYLYL GLYCOL; CARBOMER 940; CENTAUREA CYANUS FLOWER; CETOSTEARYL ALCOHOL; CHAMOMILE; PHENOXYETHANOL; BUTYLENE GLYCOL; WATER; TROLAMINE; CALENDULA OFFICINALIS FLOWER; SORBITOL

Active Incredient

Menthol, 3.0%

Purpose

Topical analgesic

Uses

temporarily relieves minor pain associated with: • arthritis • simple backache • muscle strains • sprains • bruises • cramps

Warnings

for external use only

WHEN USING

When using this prodcut•use only as directed •do not bandage tightly or use with heating pad •avoid contact with eyes or mucous membranes •do not apply to wounds or damaged skin

Stop use and ask a doctor if• condition worsens • symptoms persist for more than 7 days or clear up and occur again within a few days • redness is present • irritation develops

KEEP OUT OF REACH OF CHILDREN

If pregnant or breast-feeding, ask a health professional before use.

Keep out of reach of children. If swallowed, get medical help or contact Poison Control Center right away.

Directions:

Adults and children over 12 years:• apply generously to affected area • massage into painful area until thoroughly absorbed into skin • repeat as necessary, but no more than 4 time daily

Children 12 years or younger: ask a doctor

RECENT MAJOR CHANGES

typographical correction and effective date update

Inactive ingredients

Aloe Barbadensis Leaf Juice, Anthemis nobilis (Roman Chamomile), Arnica montana Flower Extract, Butylene Glycol, Calendula officinalis (Marigold), Caprylyl Glycol, Capsicum frutescens Fruit, Carbomer, Centaurea cyanus (Cornflower), Cetearyl Alcohol, Chamomilla recutita (Matricaria Chamomilla), Coriandrum sativum (Coriander) Fruit Oil, Emu Oil, Fragrance, Hamamelis virginiana (Witch Hazel) Bark/Leaf/Twig Extract, Hypericum perforatum (St. John's Wort), Methylsulfonylmethane, Phenoxyethanol, Purified Water, Salix alba (Willow) Bark Extract, SD Alcohol 40, Sorbitol, Tetrasodium EDTA, Tilia cordata (Lime Tree), Triethanolamine.